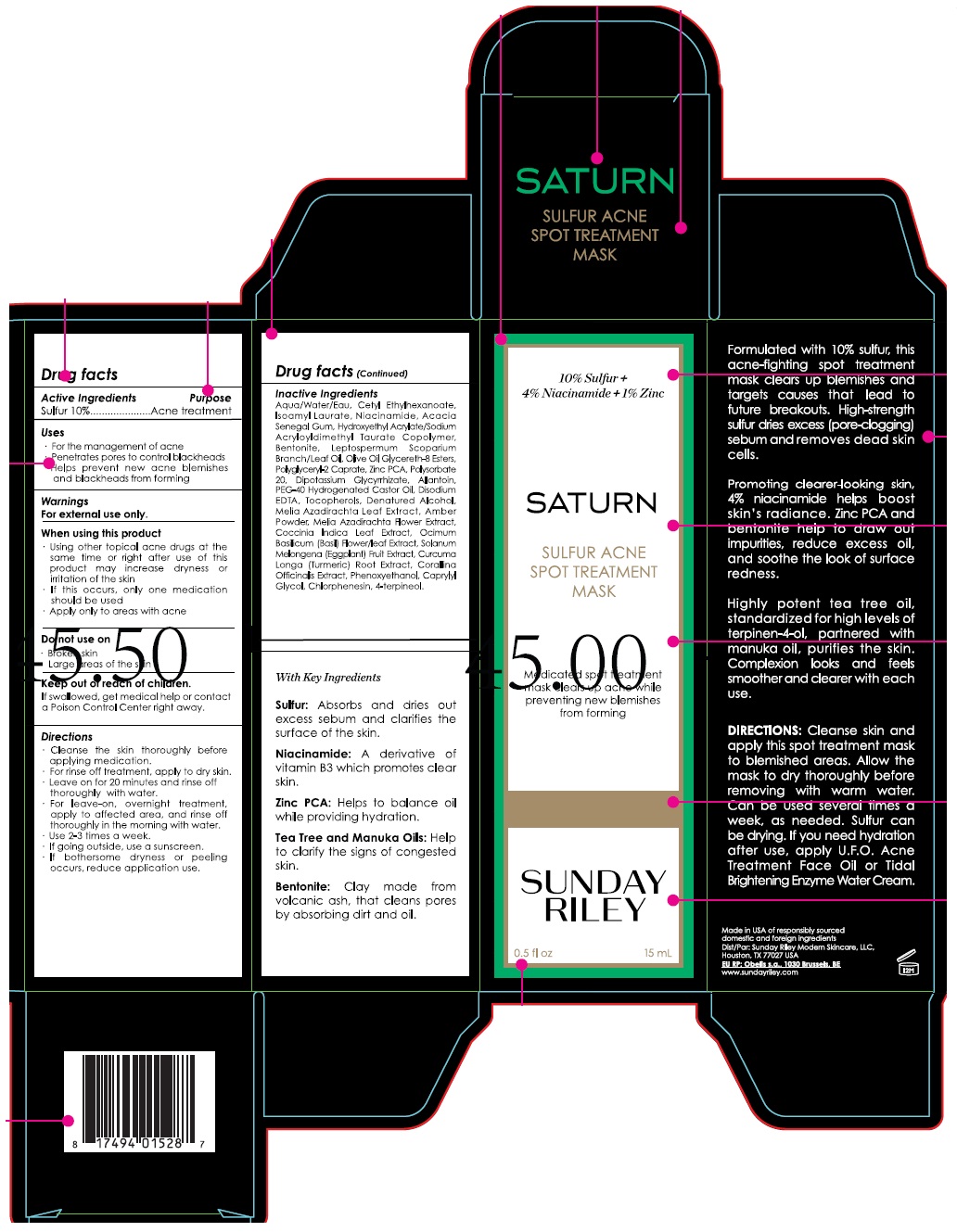 DRUG LABEL: SUNDAY RILEY SATURN SULFUR ACNE SPOT TREATMENT MASK
NDC: 73001-305 | Form: CREAM
Manufacturer: Sunday Riley Modern Skincare, LLC
Category: otc | Type: HUMAN OTC DRUG LABEL
Date: 20241226

ACTIVE INGREDIENTS: SULFUR 0.1 g/1 mL
INACTIVE INGREDIENTS: WATER; CETYL ETHYLHEXANOATE; ISOAMYL LAURATE; NIACINAMIDE; ACACIA; HYDROXYETHYL ACRYLATE/SODIUM ACRYLOYLDIMETHYL TAURATE COPOLYMER (100000 MPA.S AT 1.5%); BENTONITE; MANUKA OIL; OLIVE OIL GLYCERETH-8 ESTERS; POLYGLYCERYL-2 CAPRATE; ZINC PIDOLATE; POLYSORBATE 20; GLYCYRRHIZINATE DIPOTASSIUM; ALLANTOIN; POLYOXYL 40 HYDROGENATED CASTOR OIL; EDETATE DISODIUM ANHYDROUS; TOCOPHEROL; ALCOHOL; AZADIRACHTA INDICA LEAF; AMBER; AZADIRACHTA INDICA FLOWER; COCCINIA GRANDIS LEAF; OCIMUM BASILICUM FLOWERING TOP; EGGPLANT; TURMERIC; CORALLINA OFFICINALIS; PHENOXYETHANOL; CAPRYLYL GLYCOL; CHLORPHENESIN; 4-TERPINEOL, (+/-)-

SUNDAY RILEY SATURN SULFUR ACNE SPOT TREATMENT MASK

Active Ingredients

Sulfur 10%

Purpose

Acne treatment

Uses

• For the management of acne

• Penetrates pores to control blackheads

• Helps prevent new acne blemishes and blackheads from forming

Warnings

For external use only.

When using this product

• Using other topical acne drugs at the same time or right after use of this product may increase dryness or irritation of the skin

• If this occurs, only one medication should be used

• Apply only to areas with acne

Do not use on

• Broken skin

• Large areas of the skin

Keep out of reach of children.

If swallowed, get medical help or contact a Poison Control Center right away.

Directions

• Cleanse the skin thoroughly before applying medication.

• For rinse off treatment, apply to dry skin.

• Leave on for 20 minutes and rinse off thoroughly with water.

• For leave-on, overnight treatment, apply to affected area, and rinse off thoroughly in the morning with water.

• Use 2-3 times a week.

• If going outside, use a sunscreen.

• If bothersome dryness or peeling occurs, reduce application use.

Inactive Ingredients

Aqua/Water/Eau, Cetyl Ethyhexanoate, Isoamyl Laurate, Niacinamide, Acacia Senegal Gum, Hydroxyethyl Acrylate/Sodium Acryloyldimethyl Taurate Copolymer, Bentonite, Leptospermum Scoparium Brach/Leaf Oil, Olive Oil Glycereth-8 Esters, Polyglyceryl-2 Caprate, Zinc PCA, Polysorbate 20, Dipotassium Glycyrrhizate, Allantoin, PEG-40 Hydrogenated Castor Oil, Disodium EDTA, Tocopherols, Denatured Alcohol, Melia Azadirachta Leaf Extract, Amber Powder, Melia Azadirachta Flower Extract, Coccinia Indica Leaf Extract, Ocimum Basilicum (Basil) Flower/leaf Extract, Solanum Melongena (Eggplant) Fruit Extract, Curcuma Longa (Turmeric) Root Extract, Corallina Officinalis Extract, Phenoxyethanol, Caprylyl Glycol, Chlorphenesin, 4-terpineol.

10% Sulfur + 4% Niacinamide + 1% Zinc

Medicated spot treatment mask clears up acne while preventing new blemishes from forming

With Key Ingredients

Sulfur: Absorbs and dries out excess sebum and clarifies the surface of the skin.

Niacinamide: A derivative of Vitamin B3 which promotes clear skin.

Zinc PCA: Helps to balance oil while providing hydration.

Tea Tree and Manuka Oils: Help to clarify the signs of congested skin.

Bentonite: Clay made from volcanic ash, that cleans pores by absorbing dirt and oil.

Formulated with 10% sulfur, this acne-fighting spot treatment mask clears up blemishes and targets causes that lead to future breakouts. High-strength sulfur dries excess (pore-clogging) sebum and removes dead skin cells.

Promoting clearer-looking skin, 4% niacinamide helps boost skin's radiance. Zinc PCA and bentonite help to draw out impurities, reduce excess oil, and soothe the look of surface redness.

Highly potent tea tree oil, standardized for high levels of terpinen-4-ol, partnered with manuka oil, purifies the skin, Complexion looks and feels smoother and clearer with each use.

DIRECTIONS: Cleanse skin and apply this spot treatment mask to blemished areas. Allow the mask to dry thoroughly before removing with warm water. Can be used several times a week, as needed. sulfur can be drying. If you need hydration after use, apply U.F.O. Acne Treatment Face Oil or Tidal Brightening Enzyme Water Cream.

Made in USA of responsibly sourced domestic and foreign ingredients

Dist/Par: Sunday Riley Modern Skincare, LLC

Houston, TX 77027 USA

EU RP: Obelis s.a., 1030 Brussels, BE

www.sundayriley.com